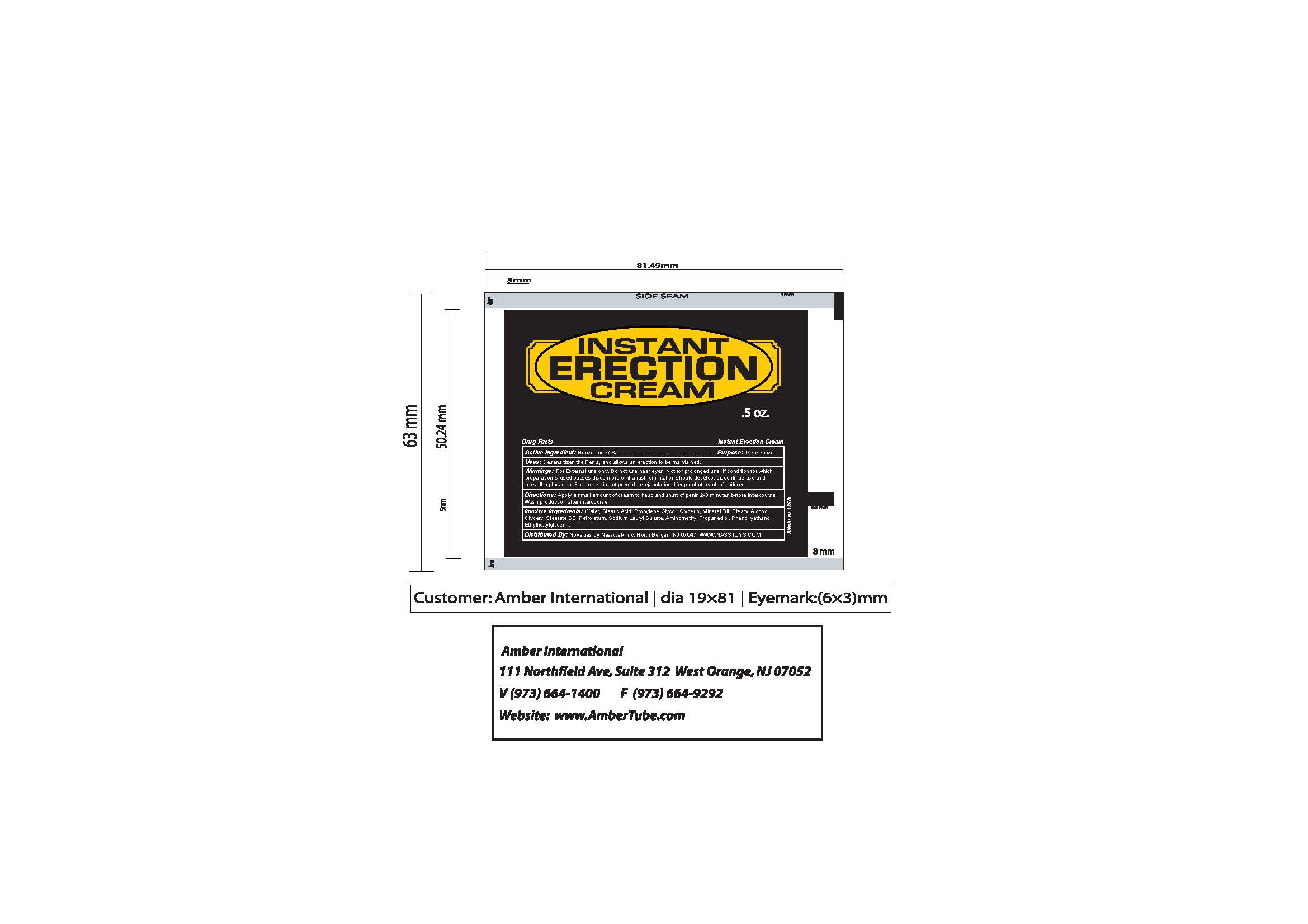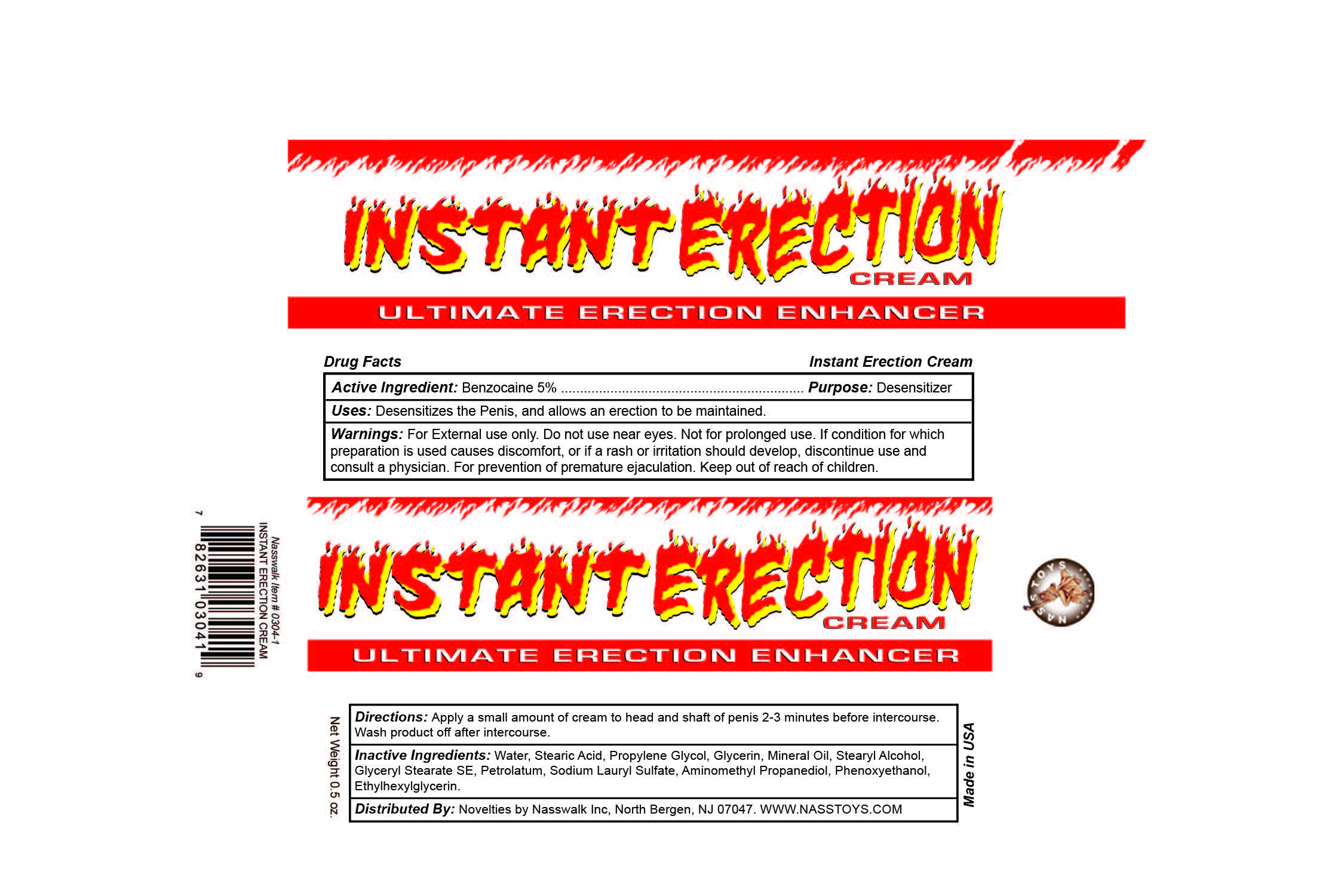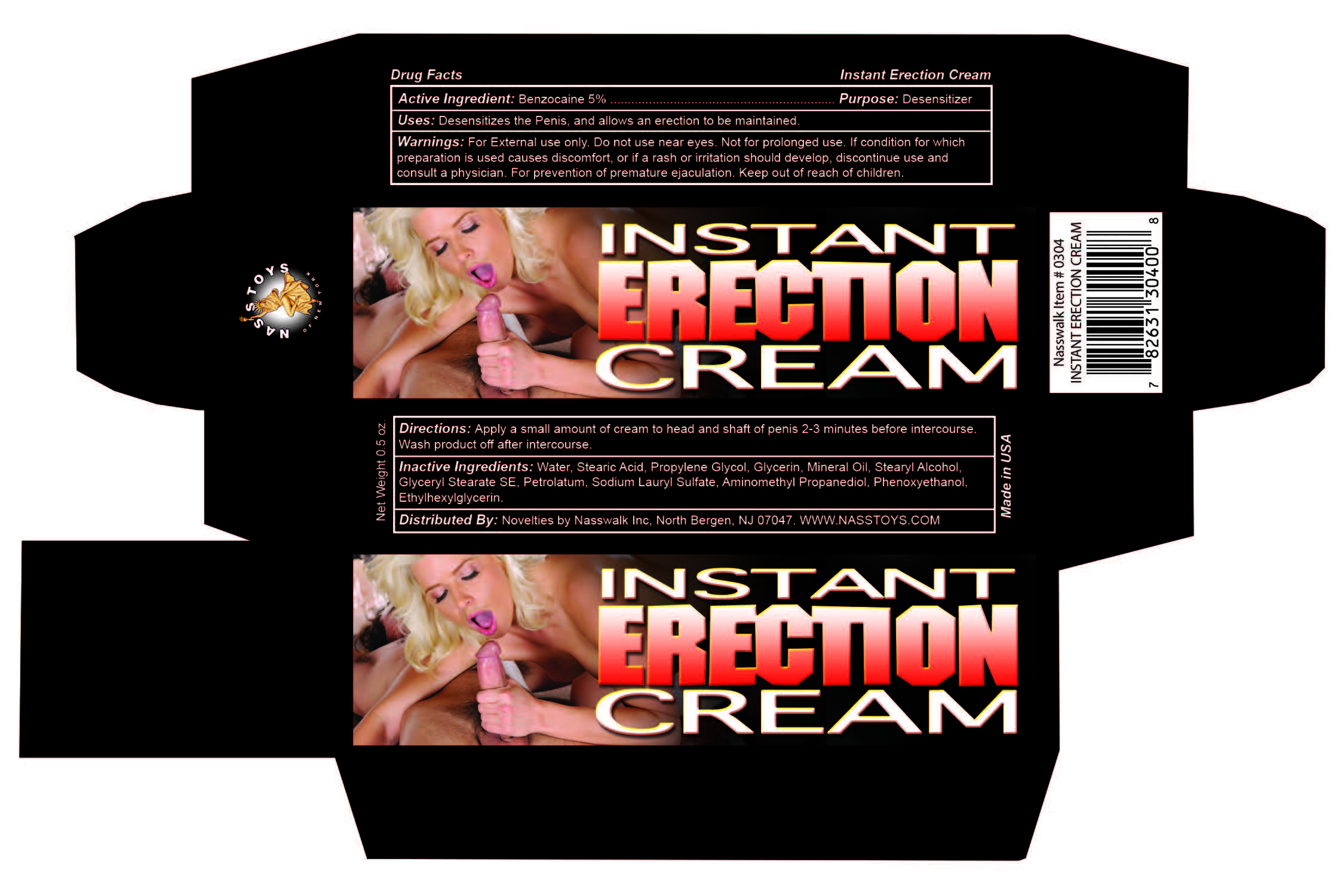 DRUG LABEL: Instant Erection
NDC: 83608-104 | Form: CREAM
Manufacturer: Novelties by Nasswalk, Inc.
Category: otc | Type: HUMAN OTC DRUG LABEL
Date: 20251110

ACTIVE INGREDIENTS: BENZOCAINE 5 g/100 mL
INACTIVE INGREDIENTS: MINERAL OIL; STEARIC ACID; PROPYLENE GLYCOL; WATER; GLYCERYL STEARATE SE; AMINOMETHYL PROPANEDIOL; ETHYLHEXYLGLYCERIN; GLYCERIN; STEARYL ALCOHOL; PETROLATUM; SODIUM LAURYL SULFATE; PHENOXYETHANOL

INSTANT ERECTION CREAM

Active Ingredient:

Benzocaine 5%

Purpose:

Desensitizer

Uses:

Desentisizes the Penis, and allows an erection to be maintained.

Warnings:

For External use only. Do not use near eyes. Not for prolonged use. If condition for which preparation is used causes discomfort, or if a rash or irritation should develop, discontinue use and consult a physician. For prevention of premature ejaculation.

Directions:

Apply a small amount of cream to head and shaft of penis 2-3 minutes before intercourse. Wash product off after intercourse.

Inactive Ingredients:

Water, Stearic Acid, Propylene Glycol, Glycerin, Mineral Oil, Stearyl Alcohol, Glyceryl Stearate SE, Petrolatum, Sodium Lauryl Sulfate, Aminomethyl Propanediol, Phenoxyethanol, Ethylhexylglycerin.

INSTANT ERECTION CREAM

ULTIMATE ERECTION ENHANCER

Net Wt. 0.5 oz.

Made in USA

Distributed By: Novelties by Nasswalk Inc, North Bergeb, NJ 07047. WWW.NASSTOYS.COM

Tube:

Carton:

INSTANT ERECTION CREAM

Net Wt. 0.5 oz.

Made in USA

Distributed By: Novelties by Nasswalk Inc, North Bergeb, NJ 07047. WWW.NASSTOYS.COM

Carton: